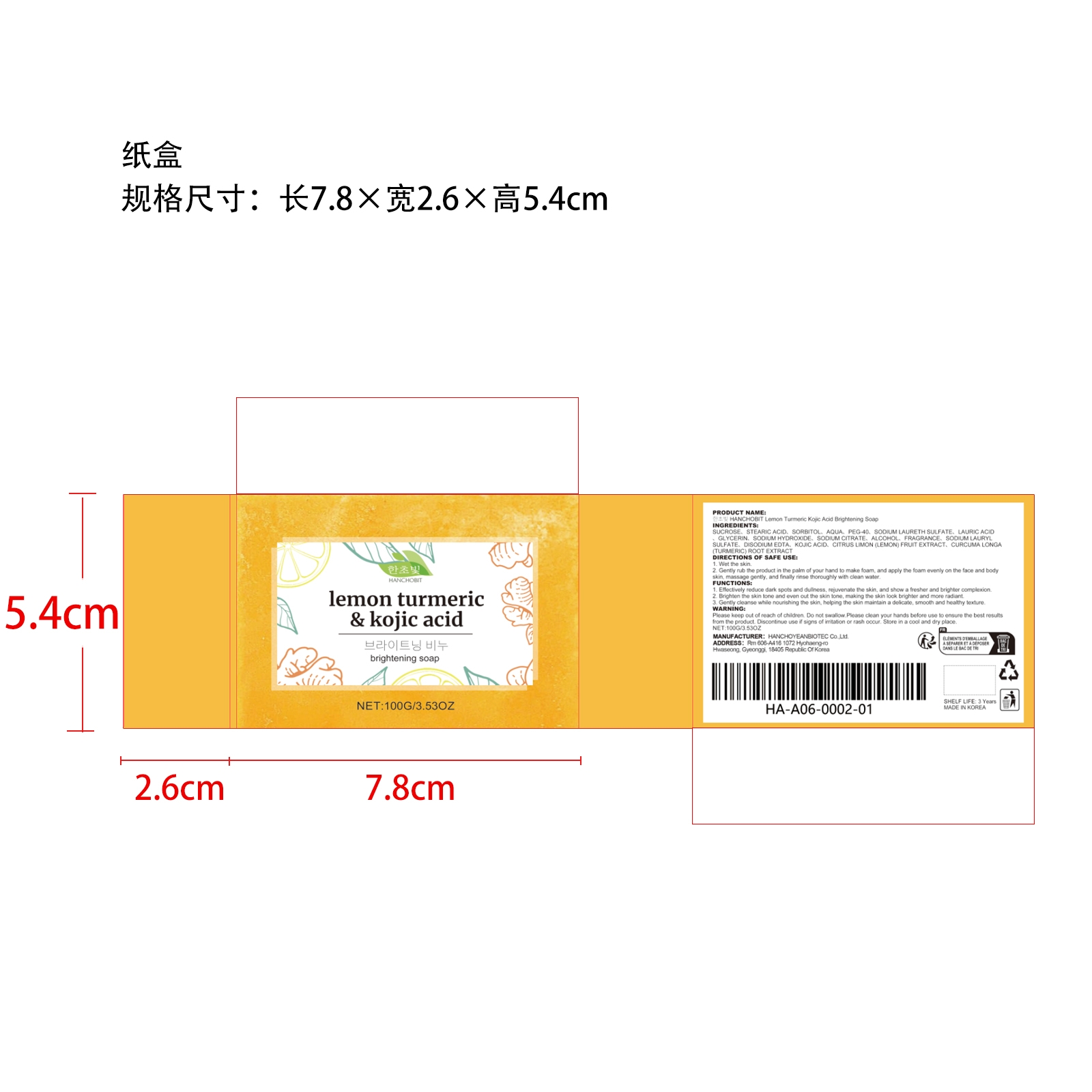 DRUG LABEL: HANCHOBIT Lemon Turmeric Kojic Acid Brightening
NDC: 85164-002 | Form: SOAP
Manufacturer: HANCHOYEANBIOTEC Co.,Ltd.
Category: otc | Type: HUMAN OTC DRUG LABEL
Date: 20251127

ACTIVE INGREDIENTS: LEMON 0.02 g/100 g; TURMERIC 0.02 g/100 g
INACTIVE INGREDIENTS: SODIUM HYDROXIDE 3 g/100 g; FRAGRANCE LEMON ORC2001060 1 g/100 g; SODIUM LAURETH SULFATE 10 g/100 g; LAURIC ACID 4 g/100 g; PEG-40 10 g/100 g; EDETATE DISODIUM 0.05 g/100 g; SORBITOL 14 g/100 g; ALCOHOL 2 g/100 g; SODIUM LAURYL SULFATE 1 g/100 g; KOJIC ACID 0.02 g/100 g; SUCROSE 20 g/100 g; STEARIC ACID 15 g/100 g; AQUA 12.89 g/100 g; SODIUM CITRATE 3 g/100 g; GLYCERIN 4 g/100 g

ACTIVE INGREDIENTS

LEMON、TURMERIC

Purpose

1. Effectively reduce dark spots and dullness, rejuvenate the skin, and show a fresher and brighter complexion.

2. Brighten the skin tone and even out the skin tone, making the skin look brighter and more radiant.

3. Gently cleanse while nourishing the skin, helping the skin maintain a delicate, smooth and healthy texture.

USE

1. Wet the skin.

2. Gently rub the product in the palm of your hand to make foam, and apply the foam evenly on the face and body skin, massage gently, and finally rinse thoroughly with clean water.

warnings

Please keep out of reach of children. Do not swallow.Please clean your hands before use to ensure the best results from the product. Discontinue use if signs of irritation or rash occur. Store in a cool and dry place.

Do not use

Discontinue use if signs of irritation or rash occur.

stop use

Discontinue use if signs of irritation or rash occur.

KEEP OUT OF REACH OF CHILDREN

Please keep out of reach of children. Do not swallow.

STORAGE AND HANDLING

Store in a cool and dry place.

INACTIVE INGREDIENT

SUCROSE、

STEARIC ACID、

SORBITOL、

AQUA、

PEG-40、

SODIUM LAURETH SULFATE、

LAURIC ACID、

GLYCERIN、

SODIUM HYDROXIDE、

SODIUM CITRATE、

ALCOHOL、

FRAGRANCE LEMON ORC2001060、

SODIUM LAURYL SULFATE、

EDETATE DISODIUM、

KOJIC ACID